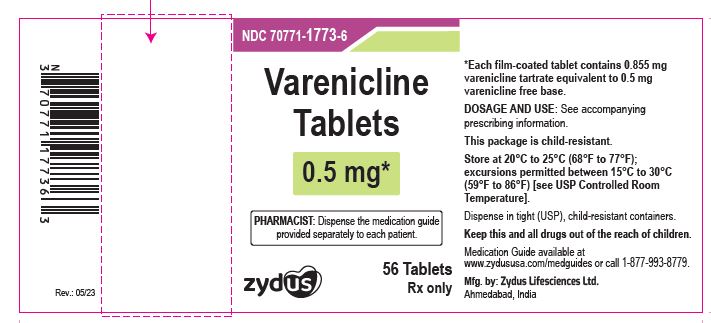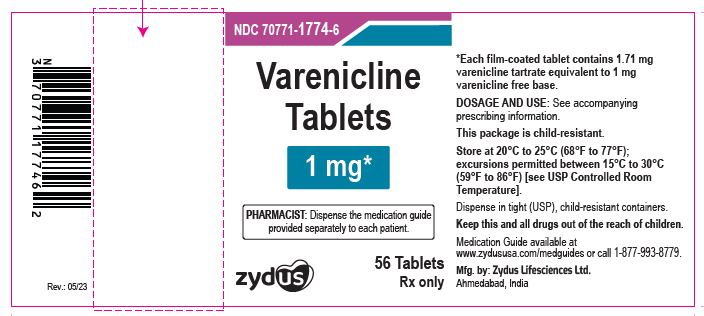 DRUG LABEL: Varenicline
NDC: 70771-1773 | Form: TABLET, FILM COATED
Manufacturer: Zydus Lifesciences Limited
Category: prescription | Type: HUMAN PRESCRIPTION DRUG LABEL
Date: 20230928

ACTIVE INGREDIENTS: VARENICLINE TARTRATE 0.5 mg/1 1
INACTIVE INGREDIENTS: ANHYDROUS DIBASIC CALCIUM PHOSPHATE; CROSCARMELLOSE SODIUM; HYPROMELLOSE 2910 (3 MPA.S); HYPROMELLOSE 2910 (6 MPA.S); MAGNESIUM STEARATE; CELLULOSE, MICROCRYSTALLINE; SILICON DIOXIDE; TITANIUM DIOXIDE; TRIACETIN

Varenicline Tablets

PACKAGE LABEL.PRINCIPAL DISPLAY PANEL

NDC 70771-1773-6

Varenicline Tablets, 0.5 mg

56 Tablets

Rx only

NDC 70771-1774-6

Varenicline Tablets, 1 mg

56 Tablets

Rx only